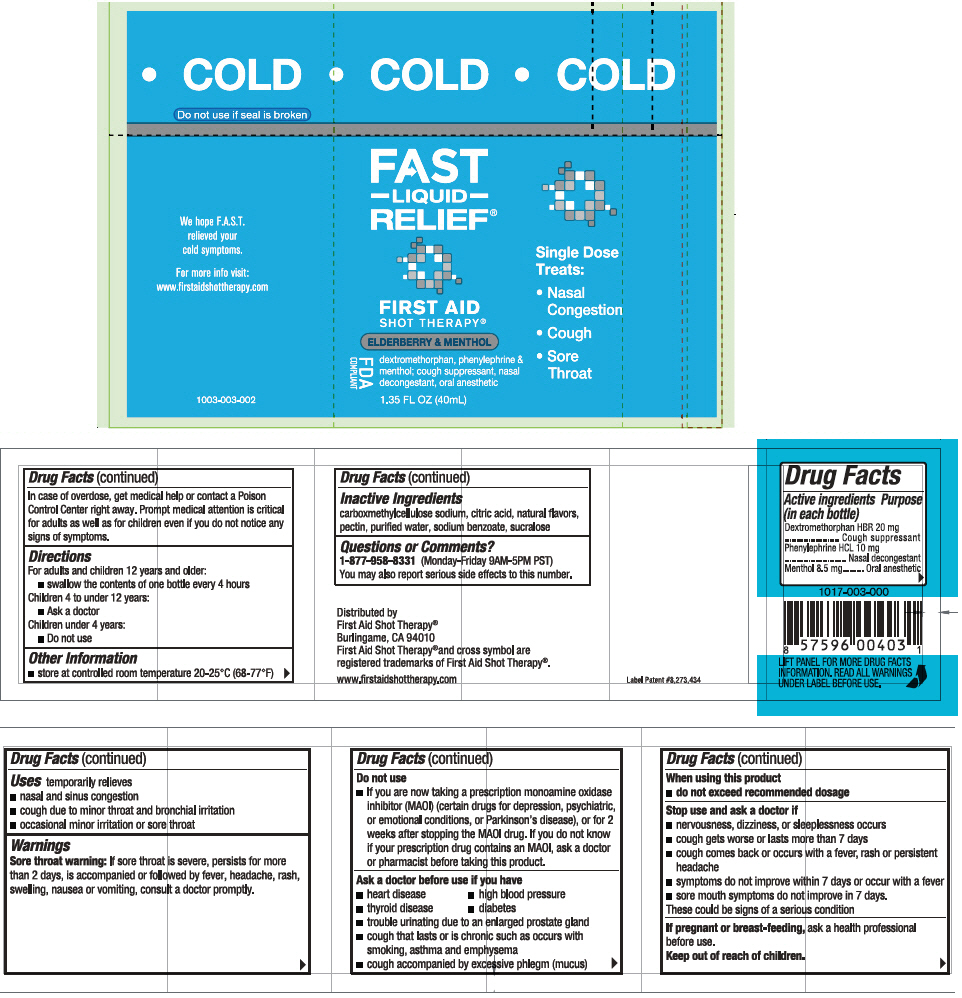 DRUG LABEL: First Aid Shot Therapy Cold Relief
NDC: 57815-031 | Form: SOLUTION
Manufacturer: First Aid Beverages, Inc.
Category: otc | Type: HUMAN OTC DRUG LABEL
Date: 20150827

ACTIVE INGREDIENTS: Dextromethorphan Hydrobromide 20 mg/40 mL; Phenylephrine Hydrochloride 10 mg/40 mL; Menthol 8.5 mg/40 mL
INACTIVE INGREDIENTS: Anhydrous Citric Acid; Carboxymethylcellulose sodium, unspecified form; Pectin; Sodium Benzoate; Sucralose; Water

First Aid Shot Therapy® Cold Relief

Drug Facts

ACTIVE INGREDIENT

PURPOSE

Active ingredients |  | Purposes
Dextromethorphan HBR 20 mg |  | Cough suppressant
Phenylephrine HCL 10 mg |  | Nasal decongestant
Menthol 8.5 mg |  | Oral anesthetic

Uses

temporarily relieves

- nasal and sinus congestion
- cough due to minor throat and bronchial irritation
- occasional minor irritation or sore throat

Warnings

Sore throat warning

If sore throat is severe, persists for more than 2 days, is accompanied or followed by fever, headache, rash, swelling, nausea or vomiting, consult a doctor promptly.

Do not use

- If you are now taking a prescription monoamine oxidase inhibitor (MAOI) (certain drugs for depression, psychiatric, or emotional conditions, or Parkinson's disease), or for 2 weeks after stopping the MAOI drug. If you do not know if your prescription drug contains an MAOI, ask a doctor or pharmacist before taking this product.

Ask a doctor before use if you have

- heart disease
- high blood pressure
- thyroid disease
- diabetes
- trouble urinating due to an enlarged prostate gland
- cough that lasts or is chronic such as occurs with smoking, asthma and emphysema
- cough accompanied by excessive phlegm (mucus)

When using this product

- do not exceed recommended dosage

Stop use and ask a doctor if

- nervousness, dizziness, or sleeplessness occurs
- cough gets worse or lasts more than 7 days
- cough comes back or occurs with a fever, rash or persistent headache
- symptoms do not improve within 7 days or occur with a fever
- sore mouth symptoms do not improve in 7 days.

These could be signs of a serious condition

PREGNANCY OR BREAST FEEDING

If pregnant or breast-feeding, ask a health care professional before use.

Keep out of reach of children.

In case of overdose, get medical help or contact a Poison Control Center right away. Prompt medical attention is critical for adults as well as for children even if you do not notice any signs of symptoms.

Directions

For adults and children 12 years and over:

- Swallow the contents of one bottle every 4 hours

Children 4 to under 12 years:

- Ask a doctor

Children under 4 years:

- Do not use

Other information

- store at controlled room temperature 20-25°C (68-77°F)

Inactive ingredients

carboxymethylcellulose sodium, citric acid, natural flavors, pectin, purified water, sodium benzoate, sucralose

Questions or comments?

1-877-958-8331 (Monday-Friday 9AM-5PM PST). You may also report serious side effects to this number.

Distributed by
First Aid Shot Therapy®
Burlingame, CA 94010

PRINCIPAL DISPLAY PANEL - 40 mL Bottle Label

COLD

FAST
–LIQUID–
RELIEF®

FIRST AID
SHOT THERAPY®

ELDERBERRY & MENTHOL

FDA
COMPLIANT

dextromethorphan, phenylephrine &
menthol; cough suppressant, nasal
decongestant, oral anesthetic

1.35 FL OZ (40mL)